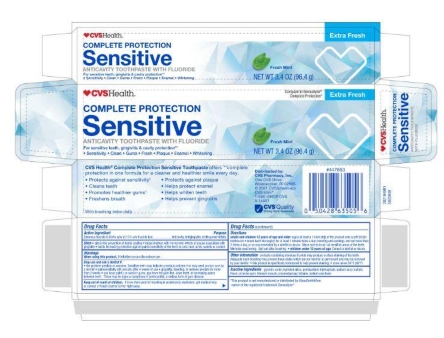 DRUG LABEL: CVS Complete Protection
NDC: 69842-549 | Form: PASTE, DENTIFRICE
Manufacturer: CVS
Category: otc | Type: HUMAN OTC DRUG LABEL
Date: 20260106

ACTIVE INGREDIENTS: STANNOUS FLUORIDE 0.15 g/100 g
INACTIVE INGREDIENTS: WATER; SACCHARIN SODIUM; TITANIUM DIOXIDE; CARBOXYMETHYLCELLULOSE SODIUM; HYDRATED SILICA; COCAMIDOPROPYL BETAINE; SODIUM LAURYL SULFATE; GLYCERIN; SODIUM TRIPOLYPHOSPHATE ANHYDROUS

5820049 CVS Complete Protection TP

ACTIVE INGREDIENT

Stannous fluoride 0.454% w/w (0.15% w/v fluoride ion)

PURPOSE

Anticavity, Antigingivitis, Antihypersensitivity

INDICATIONS AND USAGE

aids in teh prevention of dental cavities * helps interfere with the harmful effects of plaque associated with gingivitis * builds increasing protection against painful sensitivity of the teeth to cold, heat, acids, sweets or contact

When using this product, if irritation occurs discontinue use.

Stop use and ask a dentist if:

the problem persists or worsens. Sensitive teeth may indicate a serious problem that may need prompt care by a dentist * pain/sensitivity still persists after 4 weeks of use * gingivitis, bleeding, or redness persists for more than 2 weeks * you have painful or swollen gums, pus from the gum line, loose teeth, or increasing space between teeth. These may be signs or symptoms of periodontitis, a serious form of gum disease.

Keep out of reach of children. If more than used for brushing is accidentally swallowed, get medical help or contact a Poison Control Center right away.

DOSAGE AND ADMINISTRATION

adults and children 12 years of age and older: apply at least a 1-inch strip of the product onto a soft bristle toothbrush * brush teeth thoroughly for at least 1 minute twice a day (morning and evening), and not more than 3 times a day, or as recommended by a dentist or doctor. Make sure to brush all sensitive areas of the teeth. Minimize swallowing. Spit out after brushing. * children under 12 years of age: Consult a dentist or doctor.

OTHER SAFETY INFORMATION

products containing stannous fluoride may produce surface staining of the teeth. Adequate tooth brushing may prevent these stains which are not harmful or permanent and may be removed by your dentist. * this product is specifically formulated to help prevent staining. * store below 30°C (86°F)

INACTIVE INGREDIENT

glycerin, water, hydrated silica, pentasodium triphosphate, sodium lauryl sulfate, flavor, cellulose gum, titanium dioxide, cocamidopropyl betaine, sodium saccharin